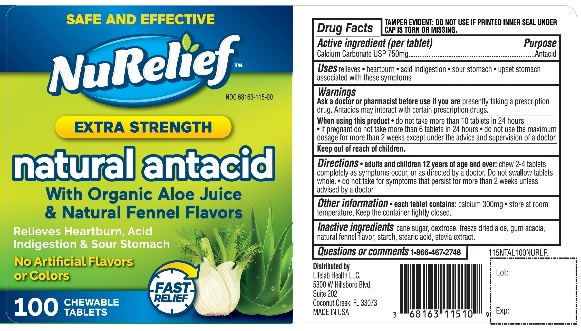 DRUG LABEL: Extra Strength Natural Antacid
NDC: 68163-115 | Form: TABLET, CHEWABLE
Manufacturer: Raritan Pharmaceuticals Inc
Category: otc | Type: HUMAN OTC DRUG LABEL
Date: 20251014

ACTIVE INGREDIENTS: CALCIUM CARBONATE 750 mg/1 1
INACTIVE INGREDIENTS: SUGARCANE; DEXTROSE, UNSPECIFIED FORM; ALOE VERA LEAF; ACACIA; STARCH, CORN; STEARIC ACID; STEVIA REBAUDIANA LEAF

NuRelief Extra Strength Natural Antacid Chewable Tablets

Active Ingredient (per tablet)

Calcium Carbonate USP 750 mg

Purpose

Antacid

Uses

relieves

- heartburn
- acid indigestion
- sour stomach
- upset stomach associated with these symptoms

Ask a doctor or pharmacist before use if you are

- presently taking a prescription drug. Antacids may interact with certain prescription drugs.

When using this product

- do not take more than 10 tablets in a 24-hour period
- if pregnant do not take more than 6 tablets in 24 hours
- do not use the maximum dosage for more than 2 weeks except under the advice and supervision of a doctor.

Directions

- adults and children 12 years of age and over:chew 2-4 tablets as symptoms occur, or as directed by a doctor.
- Do not swallow tablets whole.
- do not take for symptoms that persists for more than 2 weeks unless advised by a doctor

Other information

- each tablet contains:calcium 300 mg
- store at room temperature. Keep the container tightly closed.
- TAMPER EVIDENT: DO NOT USE IF PRINTED INNER SEAL UNDER CAP IS TORN AR MISSING

Inactive ingredients

cane sugar, dextrose, freeze dried aloe, gum acacia, flavor, starch, stearic acid, stevia extract.

Questions or comments?

1-866-467-2748

Principal Display Panel

SAFE AND EFFECTIVE

NuRelief™

NDC 68163-115-00

EXTRA STRENGTH

natural antacid

With Organic Aloe Juice & Natural Fennel Flavors

Relieves Heartburn, Acid Indigestion & Sour Stomach

No Artificial Flavors or Colors

100 CHEWABLE TABLETS

FAST RELIEF

Distributed By:

Lifelab Health LLC

5300 W Hillsboro Blvd, Suite 202

Coconut Creek, FL 33073

www.NuRelief.com

MADE IN USA